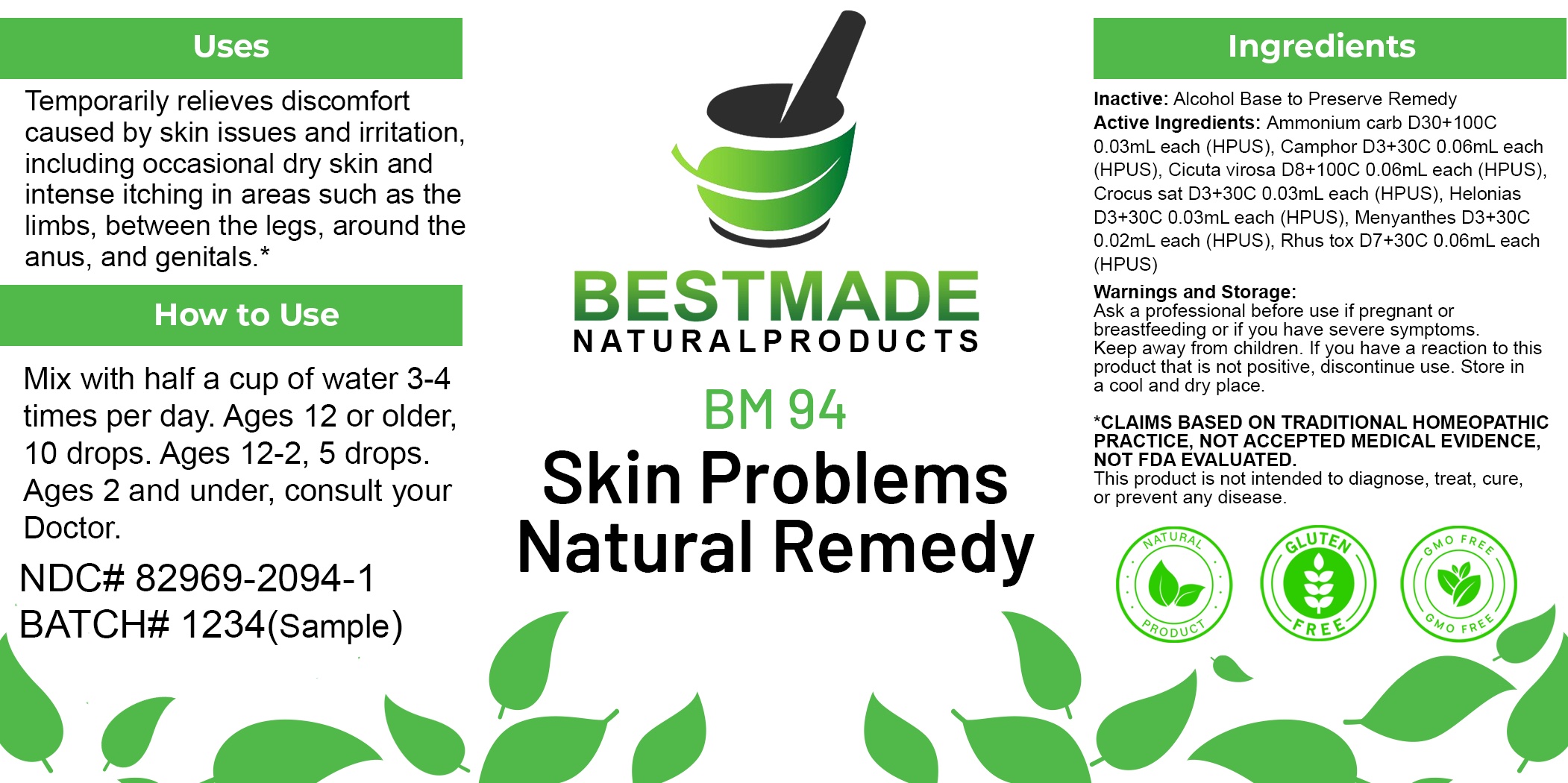 DRUG LABEL: Bestmade Natural Products BM94
NDC: 82969-2094 | Form: LIQUID
Manufacturer: Bestmade Natural Products
Category: homeopathic | Type: HUMAN OTC DRUG LABEL
Date: 20250203

ACTIVE INGREDIENTS: CICUTA VIROSA ROOT 30 [hp_C]/30 [hp_C]; SAFFRON 30 [hp_C]/30 [hp_C]; CHAMAELIRIUM LUTEUM ROOT 30 [hp_C]/30 [hp_C]; CAMPHOR (NATURAL) 30 [hp_C]/30 [hp_C]; MENYANTHES TRIFOLIATA 30 [hp_C]/30 [hp_C]; TOXICODENDRON PUBESCENS LEAF 30 [hp_C]/30 [hp_C]; AMMONIUM CARBONATE 30 [hp_C]/30 [hp_C]
INACTIVE INGREDIENTS: ALCOHOL 30 [hp_C]/30 [hp_C]

BM94

DOSAGE AND ADMINISTRATION

How to Use

Mix with half a cup of water 3-4 times per day. Ages 12 or older, 10 drops. Ages 12-2, 5 drops. Ages 2 and under, consult your Doctor.

INACTIVE INGREDIENT

Ingredients

Inactive: Alcohol Base to Preserve Remedy

ACTIVE INGREDIENT

Active Ingredients: Ammonium carb D30+100C 0.03mL each (HPUS), Camphor D3+30C 0.06mL each (HPUS), Cicuta virosa D8+100C 0.06mL each (HPUS), Crocus sat D3+30C 0.03mL each (HPUS), Helonias D3+30C 0.03mL each (HPUS), Menyanthes D3+30C 0.02mL each (HPUS), Rhus tox D7+30C 0.06mL each (HPUS).

Uses

Temporarily relieves discomfort caused by skin issues and irritation, including occasional dry skin and intense itching in areas such as the limbs, between the legs, around the anus, and genitals.*

*CLAIMS BASED ON TRADITIONAL HOMEOPATHIC PRACTICE, NOT ACCEPTED MEDICAL EVIDENCE, NOT FDA EVALUATED.

This product is not intended to diagnose, treat, cure, or prevent any disease.

Uses

Temporarily relieves discomfort caused by skin issues and irritation, including occasional dry skin and intense itching in areas such as the limbs, between the legs, around the anus, and genitals.*

*CLAIMS BASED ON TRADITIONAL HOMEOPATHIC PRACTICE, NOT ACCEPTED MEDICAL EVIDENCE, NOT FDA EVALUATED.

This product is not intended to diagnose, treat, cure, or prevent any disease.

KEEP OUT OF REACH OF CHILDREN

Warnings and Storage:

Ask a professional before use if pregnant or breastfeeding or if you have severe symptoms. Keep away from children. If you have a reaction to this product that is not positive, discontinue use. Store in a cool and dry place.

Warnings and Storage:

Ask a professional before use if pregnant or breastfeeding or if you have severe symptoms. Keep away from children. If you have a reaction to this product that is not positive, discontinue use. Store in a cool and dry place.

*CLAIMS BASED ON TRADITIONAL HOMEOPATHIC PRACTICE, NOT ACCEPTED MEDICAL EVIDENCE, NOT FDA EVALUATED.

This product is not intended to diagnose, treat, cure, or prevent any disease.

Entire package label